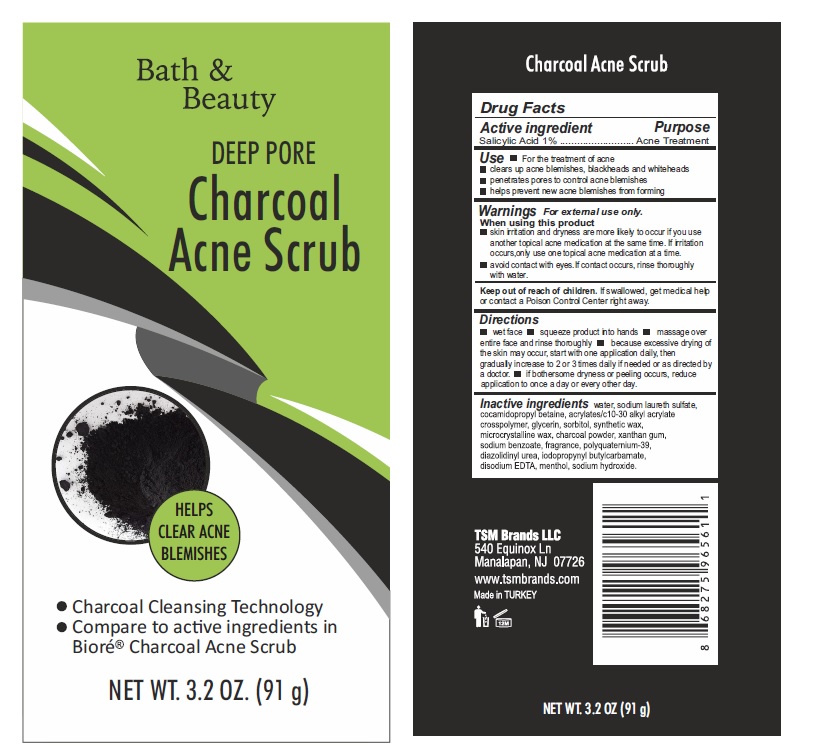 DRUG LABEL: Bath  And Beauty

NDC: 76772-025 | Form: GEL
Manufacturer: TSM ITHALAT IHRACAT SANAYI VE DIS TICARET LIMITED SIRKETI
Category: otc | Type: HUMAN OTC DRUG LABEL
Date: 20210310

ACTIVE INGREDIENTS: SALICYLIC ACID 1.3 g/91 g
INACTIVE INGREDIENTS: SODIUM LAURETH SULFATE; COCAMIDOPROPYL BETAINE; POLYQUATERNIUM-39 (22.5/51/26.5 ACRYLIC ACID/ACRYLAMIDE/DADMAC; 1600000 MW); CARBOMER INTERPOLYMER TYPE A (ALLYL SUCROSE CROSSLINKED); WATER; SORBITOL; GLYCERIN; SYNTHETIC WAX (1200 MW); MICROCRYSTALLINE WAX; SODIUM HYDROXIDE; XANTHAN GUM; MENTHOL; CARBOMER COPOLYMER TYPE A; SODIUM BENZOATE; ACTIVATED CHARCOAL; EDETATE DISODIUM

Bath & Beauty Deep Pore Charcoal Acne Scrub

Active ingredient

Salicylic acid 1%

Purpose

Acne treatment

Uses

- clears up acne blemishes
- penetrates pores to control acne blemishes
- helps prevent new acne blemishes from forming
- For the treatment of acne

Warnings

For external use only.

When using this product

- avoid contact with eyes. If contact occurs, rinse thoroughly with water.
- skin irritation and dryness are more likely to occur if you use another topical acne medication at the same time.
- If irritation occurs, only use one topical acne medication at a time.

Keep out of reach of children. If swallowed, get medical help or contact a Poison Control Center right away.

Directions

- Wet face
- Squeeze product into hands
- Massage over entire face and rinse thoroughly
- Because excessive drying of gradually increase to 2 or 3 times daily if needed or as directed by a doctor.
- If bothersome dryness or peeling occurs, reduce application to once a day or every other day.

Other information

store at room temperature

Inactive ingredients

Water, Glycerin, Sodium laureth Sulfate, Cocamidopropyl Betaine, Sorbitol, Synthetic Wax, Microcrystalline Wax, Charcola Powder , Xanthan gum, fragrance, Sodium hydroxide, menthol, polyquaternium-39, charcoal powder, Disodium EDTA, Iodopropynyl Butylcarbamate, Sodium Benzoate